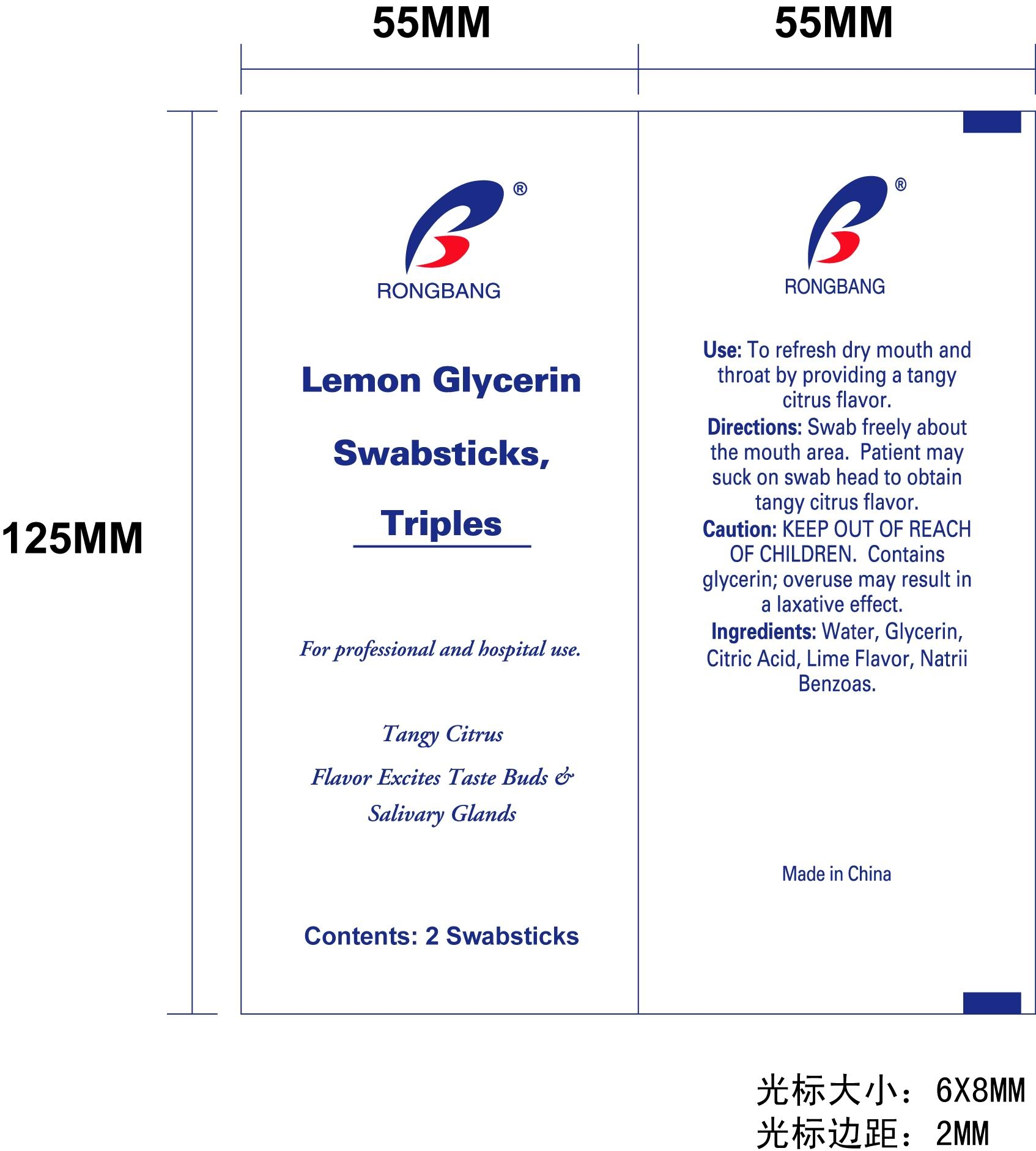 DRUG LABEL: Lemon Glycerin
NDC: 49953-1894 | Form: SWAB
Manufacturer: Dalian Rongbang Medical Healthy Devices Co
Category: otc | Type: HUMAN OTC DRUG LABEL
Date: 20101001

ACTIVE INGREDIENTS: GLYCERIN 0.43 mL/10 mL
INACTIVE INGREDIENTS: water; CITRIC ACID MONOHYDRATE

Lemon Glycerin Swabs

DOSAGE AND ADMINISTRATION

two swabsticks

swab freely about the mouth area. patient may suck on swab head to obtain tangy citrus flavor

INACTIVE INGREDIENT

water, citric acid, lime flavor, natrii benzoas

INDICATIONS AND USAGE

To refresh dry mouth and throat by providing a tangy citrus flavor.

Keep out of reach of children. Contains glycerin; overuse may result in a laxative effect.

ACTIVE INGREDIENT

Glycerine

WARNINGS

Contains glycerin; overuse may result in a laxative effect.

PURPOSE

To refresh dry mouth and throat.

PACKAGE LABEL

Lemon glycerin swabsticks, triples. For professional and hospital use.